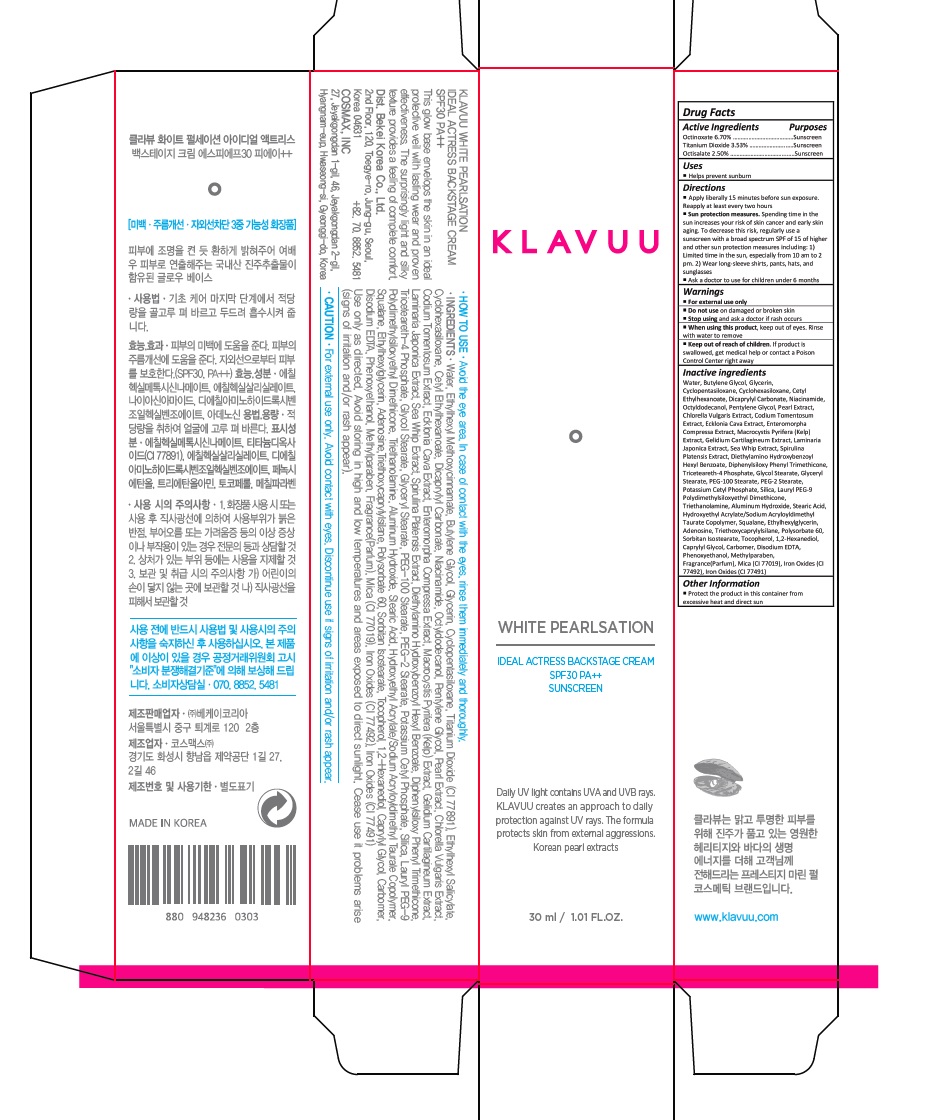 DRUG LABEL: KLAVUU WHITE PEARLSATION Ideal Actress Backstage Cream SPF30
NDC: 70976-002 | Form: CREAM
Manufacturer: Bekeikorea
Category: otc | Type: HUMAN OTC DRUG LABEL
Date: 20181030

ACTIVE INGREDIENTS: OCTINOXATE 2.01 mg/30 mL; TITANIUM DIOXIDE 1.06 mg/30 mL; OCTISALATE 0.075 mg/30 mL
INACTIVE INGREDIENTS: WATER; BUTYLENE GLYCOL; GLYCERIN; CYCLOMETHICONE 5; CYCLOMETHICONE 6; CETYL ETHYLHEXANOATE; DICAPRYLYL CARBONATE; NIACINAMIDE; OCTYLDODECANOL; PENTYLENE GLYCOL; DIETHYLAMINO HYDROXYBENZOYL HEXYL BENZOATE; DIPHENYLSILOXY PHENYL TRIMETHICONE; TRICETEARETH-4 PHOSPHATE; GLYCOL STEARATE; PHENOXYETHANOL; GLYCERYL MONOSTEARATE; PEG-100 STEARATE; PEG-2 STEARATE; POTASSIUM CETYL PHOSPHATE; SILICON DIOXIDE; MICA; CARBOXYPOLYMETHYLENE; LAURYL PEG-9 POLYDIMETHYLSILOXYETHYL DIMETHICONE; TROLAMINE; ALUMINUM HYDROXIDE; STEARIC ACID; HYDROXYETHYL ACRYLATE/SODIUM ACRYLOYLDIMETHYL TAURATE COPOLYMER (100000 MPA.S AT 1.5%); SQUALANE; ETHYLHEXYLGLYCERIN; ADENOSINE; TRIETHOXYCAPRYLYLSILANE; FERRIC OXIDE YELLOW; FERRIC OXIDE RED; EDETATE DISODIUM; POLYSORBATE 60; SORBITAN ISOSTEARATE; PEARL (HYRIOPSIS CUMINGII); CODIUM TOMENTOSUM; ECKLONIA CAVA; ULVA COMPRESSA; MACROCYSTIS PYRIFERA; GELIDIUM CARTILAGINEUM; LAMINARIA JAPONICA; TOCOPHEROL; PSEUDOPTEROGORGIA ELISABETHAE; CHLORELLA VULGARIS; SPIRULINA PLATENSIS; 1,2-HEXANEDIOL; CAPRYLYL GLYCOL; METHYLPARABEN

70976-002_KLAVUU WHITE PEARLSATION Ideal Actress Backstage Cream SPF30

ACTIVE INGREDIENT

Octinoxate 6.70%
Titanium Dioxide 3.53%
Octisalate 2.50%

PURPOSE

Sunscreen

INDICATIONS AND USAGE

Helps prevent sunburn

DOSAGE AND ADMINISTRATION

Apply liberally 15 minutes before sun exposure. Reapply at least every two hours

Sun protection measures. Spending time in the sun increases your risk of skin cancer and early skin aging. To decrease this risk, regularly use a sunscreen with a broad spectrum SPF of 15 of higher and other sun protection measures including: 1) Limited time in the sun, especially from 10 am to 2 pm. 2) Wear long-sleeve shirts, pants, hats, and sunglasses

Ask a doctor to use for children under 6 months

WARNINGS

For external use only

Do not use on damaged or broken skin

When using this product, keep out of eyes. Rinse with water to remove.

Stop using and ask a doctor if rash occurs.

KEEP OUT OF REACH OF CHILDREN

Keep out of reach of the children. If product is swallowed, get medical help or contact a poison control center right away.

INACTIVE INGREDIENT

Water, Butylene Glycol, Glycerin, Cyclopentasiloxane, Cyclohexasiloxane, Cetyl Ethylhexanoate, Dicaprylyl Carbonate, Niacinamide, Octyldodecanol, Pentylene Glycol, Pearl Extract, Chlorella Vulgaris Extract, Codium Tomentosum Extract, Ecklonia Cava Extract, Enteromorpha Compressa Extract, Macrocystis Pyrifera (Kelp) Extract, Gelidium Cartilagineum Extract, Laminaria Japonica Extract, Sea Whip Extract, Spirulina Platensis Extract, Diethylamino Hydroxybenzoyl Hexyl Benzoate, Diphenylsiloxy Phenyl Trimethicone, Triceteareth-4 Phosphate, Glycol Stearate, Glyceryl Stearate, PEG-100 Stearate, PEG-2 Stearate, Potassium Cetyl Phosphate, Silica, Lauryl PEG-9 Polydimethylsiloxyethyl Dimethicone, Triethanolamine, Aluminum Hydroxide, Stearic Acid, Hydroxyethyl Acrylate/Sodium Acryloyldimethyl Taurate Copolymer, Squalane, Ethylhexylglycerin, Adenosine, Triethoxycaprylylsilane, Polysorbate 60, Sorbitan Isostearate, Tocopherol, 1,2-Hexanediol, Caprylyl Glycol, Carbomer, Disodium EDTA, Phenoxyethanol, Methylparaben, Fragrance(Parfum), Mica (CI 77019), Iron Oxides (CI 77492), Iron Oxides (CI 77491)